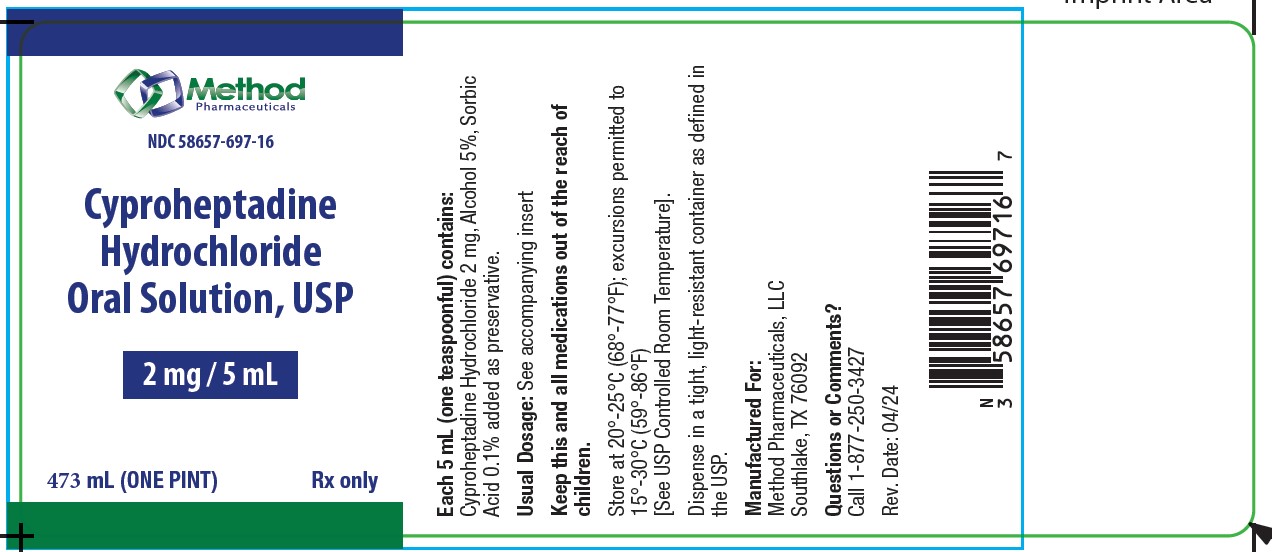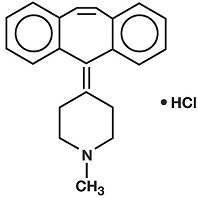 DRUG LABEL: cyproheptadine hydrochloride solution
NDC: 58657-697 | Form: SOLUTION
Manufacturer: Method Pharmaceuticals, LLC
Category: prescription | Type: HUMAN PRESCRIPTION DRUG LABEL
Date: 20251021

ACTIVE INGREDIENTS: CYPROHEPTADINE 2 mg/5 mL
INACTIVE INGREDIENTS: ALCOHOL; ANHYDROUS CITRIC ACID; D&C YELLOW NO. 10; SUCROSE; WATER; TRISODIUM CITRATE DIHYDRATE; SORBIC ACID; PEPPERMINT

DESCRIPTION

Each 5 mL (one teaspoonful) contains: Cyproheptadine Hydrochloride 2 mg

nactive ingredients:Alcohol 5%, citric acid, D&C Yellow #10, flavors, purified water, sodium citrate, sorbic acid
(0.1% as preservative) and sucrose.

Cyproheptadine Hydrochloride is an antihistaminic and antiserotonergic agent. Cyproheptadine hydrochloride is a white to slightly yellowish, crystalline solid, with a molecular weight of 350.88, which is slightly soluble in water, freely soluble in methanol, sparingly soluble in ethanol, soluble in chloroform and practically insoluble in ether. It is the sesquihydrate of 4-(5H-Dibenzo [ a,d]cyclohepten-5-ylidene)-1-methylpiperidine hydrochloride. The molecular formula of the anhydrous salt is C21H21N • HCl and the structural formula of the anhydrous salt is:

CLINICAL PHARMACOLOGY

Cyproheptadine is a serotonin and histamine antagonist with anticholinergic and sedative effects. Antiserotonin and antihistamine drugs appear to compete with serotonin and histamine, respectively, for receptor sites.

Pharmacokinetics and Metabolism:

After a single 4 mg oral dose of^14C-labeled cyproheptadine hydrochloride in normal subjects, given as tablets or syrup, 2-20% of the radioactivity was excreted in the stools. Only about 34% of the stool radioactivity was unchanged drug, corresponding to less than 5.7% of the dose. At least 40% of the administered radioactivity was excreted in the urine. No detectable amounts of unchanged drug were present in the urine of patients on chronic 12-20 mg daily doses of cyproheptadine syrup. The principal metabolite found in human urine has been identified as a quaternary ammonium glucuronide conjugate of cyproheptadine. Elimination is diminished in renal insufficiency.

INDICATIONS AND USAGE

Perennial and seasonal allergic rhinitis

Vasomotor rhinitis

Allergic conjunctivitis due to inhalant allergens and foods

Mild, uncomplicated allergic skin manifestations of urticaria and angioedema

Amelioration of allergic reactions to blood or plasma

Cold urticaria

Dermatographism

As therapy for anaphylactic reactions adjunctiveto epinephrine and other standard measures after the acute manifestations have been controlled.

CONTRAINDICATIONS

Newborn or Premature Infants:This drug should notbe used in newborn or premature infants.

Nursing Mothers:Because of the higher risk of antihistamines for infants generally and for newborns and prematures in particular, antihistamine therapy is contraindicated in nursing mothers.

Other Conditions:

Hypersensitivity to cyproheptadine and other drugs of similar chemical structure

Monoamine oxidase inhibitor therapy (see Drug Interactions)

Angle-closure glaucoma

Stenosing peptic ulcer

Symptomatic prostatic hypertrophy

Bladder neck obstruction

Pyloroduodenal obstruction

Elderly, debilitated patients

WARNINGS

Children:Overdosage of antihistamines, particularly in infants and children, may produce hallucinations, central nervous system depression, convulsions and death.

Antihistamines may diminish mental alertness; conversely, particularly in the young child, they may occasionally produce excitation.

CNS Depressants:Antihistamines may have additive effects with alcohol and other CNS depressants, e.g., hypnotics, sedatives, tranquilizers, antianxiety agents.

Activities Requiring Mental Alertness:Patients should be warned about engaging in activities requiring mental alertness and motor coordination, such as driving a car or operating machinery.

Antihistamines are more likely to cause dizziness, sedation and hypotension in elderly patients.

PRECAUTIONS

General:

Cyproheptadine has an atropine-like action and, therefore, should be used with caution in patients with:

History of bronchial asthma

Increased intraocular pressure

Hyperthyroidism

Cardiovascular disease

Hypertension

Information for Patients:

Antihistamines may diminish mental alertness; conversely, particularly in the young child, they may occasionally produce excitation. Patients should be warned about engaging in activities requiring mental alertness and motor coordination, such as driving a car or operating machinery.

Drug Interactions:

MAO inhibitors prolong and intensify the anticholinergic effects of antihistamines. Antihistamines may have additive effects with alcohol and other CNS depressants, e.g., hypnotics, sedatives, tranquilizers, antianxiety agents.

Carcinogenesis, Mutagenesis, Impairment of Fertility:

Long-term carcinogenic studies have not been done with cyproheptadine. Cyproheptadine had no effect on fertility in a two-litter study in rats or a two-generation study in mice at about 10 times the human dose. Cyproheptadine did not produce chromosome damage in human lymphocytes or fibroblasts in vitro; high doses (10-4M) were cytotoxic. Cyproheptadine did not have any mutagenic effect in the Ames microbial mutagen test; concentrations of above 500 mcg/plate inhibited bacterial growth.

Pregnancy:

Pregnancy Category B. Reproduction studies have been performed in rabbits, mice and rats at oral or subcutaneous doses up to 32 times the maximum recommended human oral dose and have revealed no evidence of impaired fertility or harm to the fetus due to cyproheptadine. Cyproheptadine has been shown to be fetotoxic in rats when given by intraperitoneal injection in doses four times the maximum recommended human oral dose. Two studies in pregnant women, however, have not shown that cyproheptadine increases the risk of abnormalities when administered during the first, second and third trimesters of pregnancy. No teratogenic effects were observed in any of the newborns. Nevertheless, because the studies in humans cannot rule out the possibility of harm, cyproheptadine should be used during pregnancy only if clearly needed.

Nursing Mothers:

It is not known whether this drug is excreted in human milk. Because many drugs are excreted in human milk, and because of the potential for serious adverse reactions in nursing infants from cyproheptadine, a decision should be made whether to discontinue nursing or to discontinue the drug, taking into account the importance of the drug to the mother (see CONTRAINDICATIONS).

Pediatric Use:

Safety and effectiveness in pediatric patients below the age of two years have not been established. (See CONTRAINDICATIONS, Newborn or Premature Infants, and WARNINGS, Children.)

ADVERSE REACTIONS

Adverse reactions which have been reported with the use of antihistamines are as follows:

Central Nervous System:Sedation and sleepiness (often transient), dizziness, disturbed coordination, confusion, restlessness, excitation, nervousness, tremor, irritability, insomnia, paresthesias, neuritis, convulsions, euphoria, hallucinations, hysteria, faintness.

Integumentary:Allergic manifestation of rash and edema, excessive perspiration, urticaria, photosensitivity.

Special Senses:Acute labyrinthitis, blurred vision, diplopia, vertigo, tinnitus.

Cardiovascular:Hypotension, palpitation, tachycardia, extrasystoles, anaphylactic shock.

Hematologic:Hemolytic anemia, leukopenia, agranulocytosis, thrombocytopenia.

Digestive System:Dryness of mouth, epigastric distress, anorexia, nausea, vomiting, diarrhea, constipation, jaundice.

Genitourinary:Urinary frequency, difficult urination, urinary retention, early menses.

Respiratory:Dryness of nose and throat, thickening of bronchial secretions, tightness of chest and wheezing, nasal stuffiness.

Miscellaneous:Fatigue, chills, headache, increased appetite/weight gain.

OVERDOSAGE

Antihistamine overdosage reactions may vary from central nervous system depression to stimulation especially in children. Also, atropine-like signs and symptoms (dry mouth; fixed, dilated pupils; flushing, etc.) as well as gastrointestinal symptoms may occur.

If vomiting has not occurred spontaneously,the patient should be induced to vomit with syrup of ipecac.

If the patient is unable to vomit,perform gastric lavage followed by activated charcoal. Isotonic or ½ isotonic saline is the lavage of choice. Precautions against aspiration must be taken especially in infants and children.

When life-threatening CNS signs and symptoms are present, intravenous physostigmine salicylate may be considered. Dosage and frequency of administration are dependent on age, clinical response and recurrence after response. (See package circulars for physostigmine products.)

Saline cathartics,as milk of magnesia, by osmosis draw water into the bowel and, therefore, are valuable for their action in rapid dilution of bowel content.

Stimulantsshould notbe used. Vasopressors may be used to treat hypotension.

The oral LD50 of cyproheptadine is 123 mg/kg, and 295 mg/kg in the mouse and rat, respectively.

DOSAGE AND ADMINISTRATION

DOSAGE SHOULD BE INDIVIDUALIZED ACCORDING TO THE NEEDS AND THE RESPONSE OF THE PATIENT.

Although intended primarily for administration to children, the syrup is also used for administration to adults who cannot swallow tablets.

Children:The total daily dosage for children may be calculated on the basis of body weight or body area using approximately 0.25 mg/kg/day (0.11 mg/lb/day) or 8 mg per square meter of body surface (8 mg/m^2).

Age 2 to 6 years: The usual dose is 2 mg (one teaspoonful) two or three times a day, adjusted as necessary to the size and response of the patient. The dose is not to exceed 12 mg a day.

Age 7 to 14 years: The usual dose is 4 mg (two teaspoonsful) two or three times a day, adjusted as necessary to the size and response of the patient. The dose is not to exceed 16 mg a day.

Adults:The total daily dose for adults should not exceed 0.5 mg/kg/day (0.23 mg/lb/day). The therapeutic range is 4 to 20 mg a day, with the majority of patients requiring 12 to 16 mg a day. An occasional patient may require as much as 32 mg a day for adequate relief. It is suggested that dosage be initiated with 4 mg (two teaspoonsful) three times a day and adjusted according to the size and response of the patient.

HOW SUPPLIED

Cyproheptadine Hydrochloride Oral Solution, USP, 2 mg/5 mL in a yellow, peppermint-flavored vehicle, is supplied in a pint (473 mL) container.

Store at 20°-25°C (68°-77°F) excursion permitted to 15°-30°C (59°-86°F) [See USP Controlled Room Temperature].

Dispense in a tight, light-resistant container as defined in the USP.

NDC # 58657-697-16

Manufactured for:
Method Pharmaceuticals, LLC
Southlake, TX 76092
Questions or Comments?
Call 1-877-250-3427
Rev. Date: 04/2024

PACKAGE LABEL. PRINCIPAL DISPLAY PANEL

Cyproheptadine Hydrochloride Oral Solution, USP

NDC58657-697-16